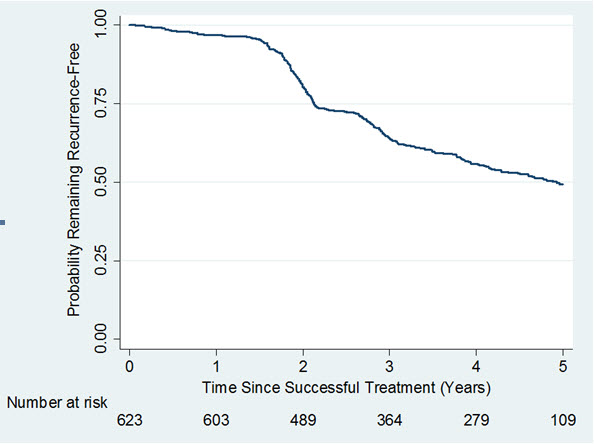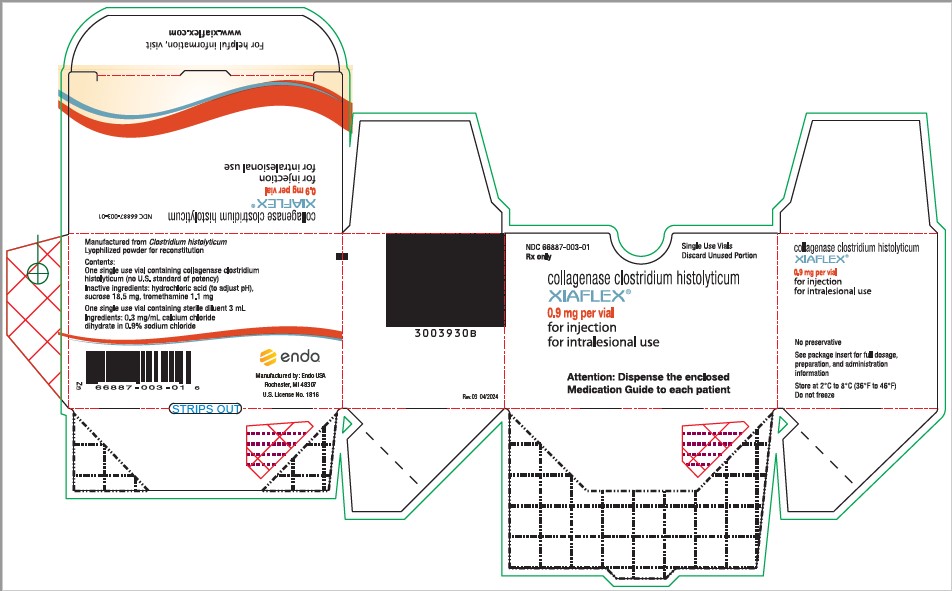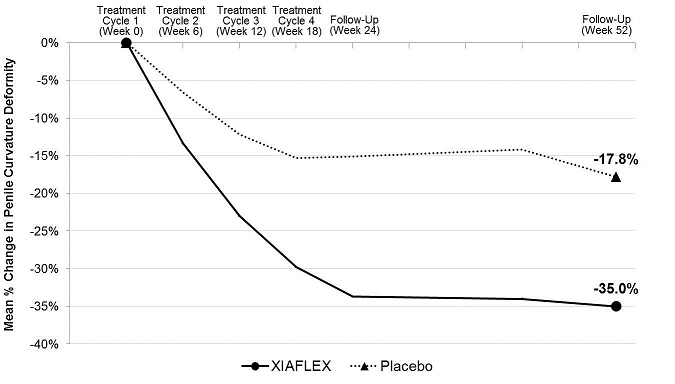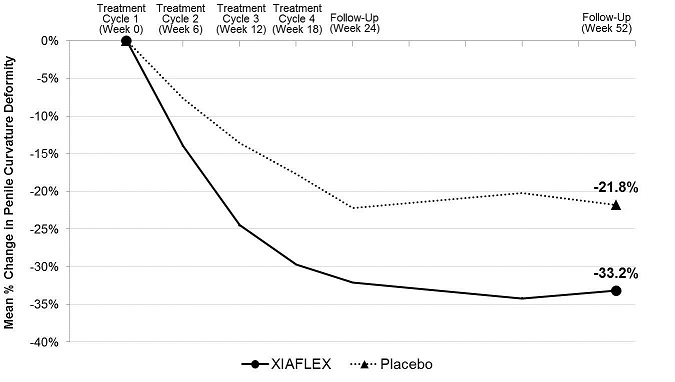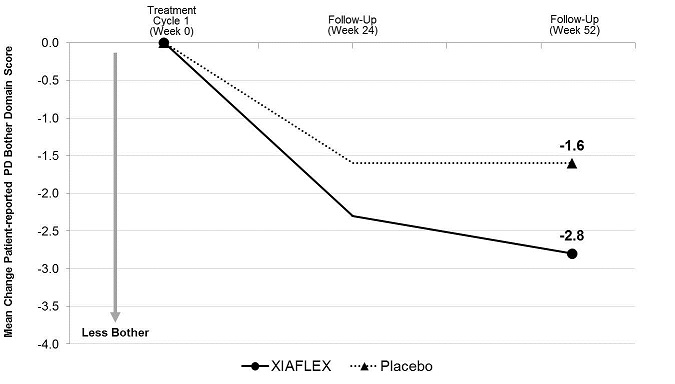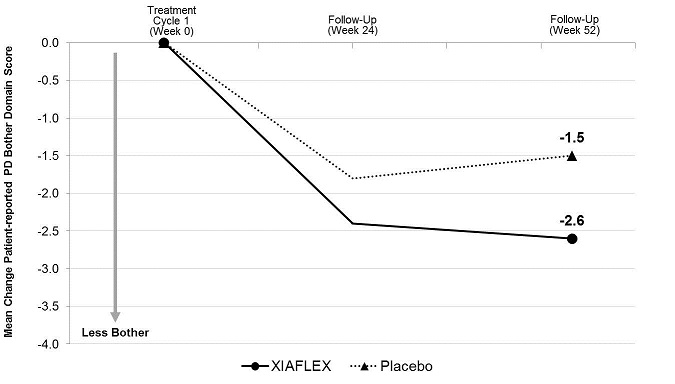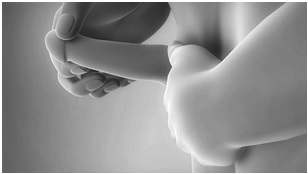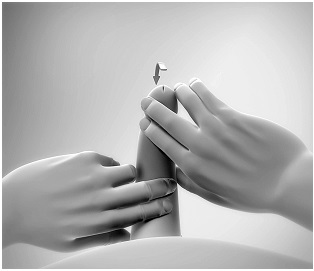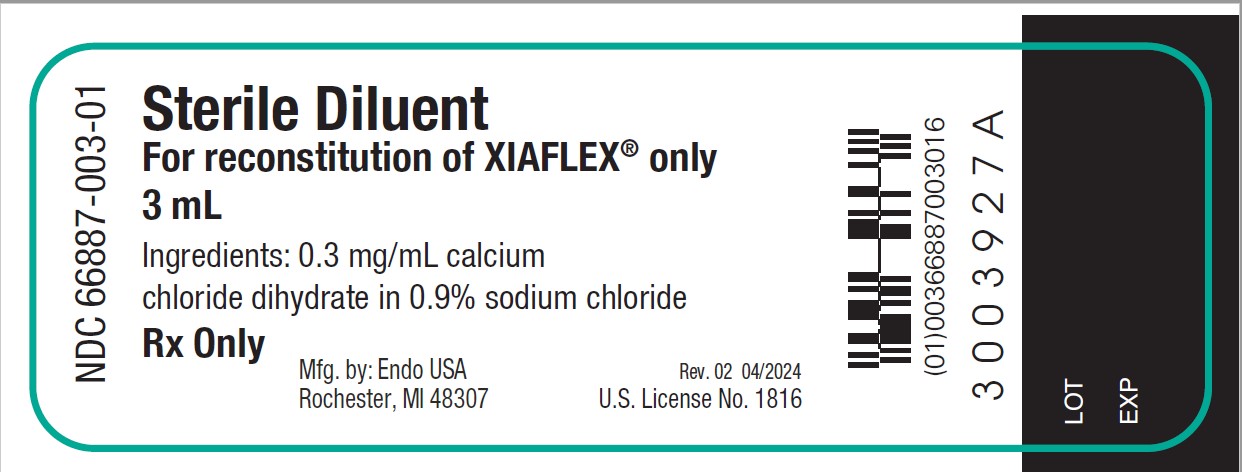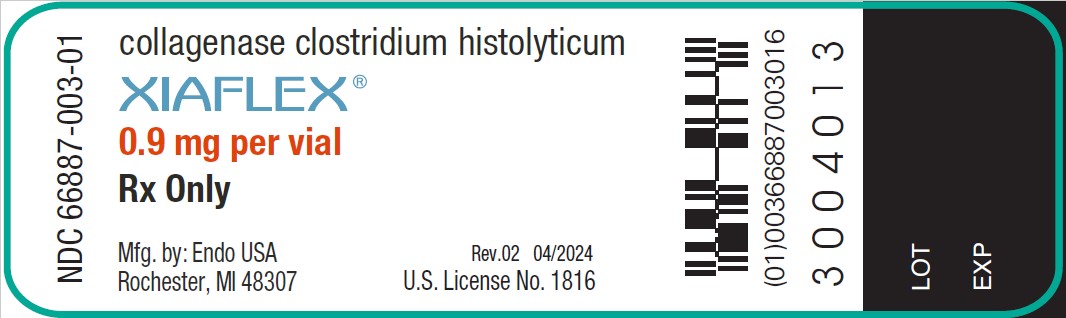 DRUG LABEL: XIAFLEX
NDC: 66887-003 | Form: KIT | Route: INTRALESIONAL
Manufacturer: ENDO USA, Inc.
Category: prescription | Type: HUMAN PRESCRIPTION DRUG LABEL
Date: 20240405

ACTIVE INGREDIENTS: COLLAGENASE CLOSTRIDIUM HISTOLYTICUM 0.9 mg/1 1
INACTIVE INGREDIENTS: HYDROCHLORIC ACID 0.5 mg/1 1; SUCROSE 18.5 mg/1 1; TROMETHAMINE 1.1 mg/1 1; CALCIUM CHLORIDE 0.9 mg/3 mL; SODIUM CHLORIDE; WATER

HIGHLIGHTS OF PRESCRIBING INFORMATION

These highlights do not include all the information needed to use XIAFLEX safely and effectively. See full prescribing information for XIAFLEX.
XIAFLEX® (collagenase clostridium histolyticum) for injection, for intralesional use
Initial U.S. Approval: 2010

WARNING: CORPORAL RUPTURE (PENILE FRACTURE) OR OTHER SERIOUS PENILE INJURY IN THE TREATMENT OF PEYRONIE’S DISEASE

See full prescribing information for complete boxed warning

- Corporal rupture (penile fracture) was reported as an adverse reaction in 5 of 1044 (0.5%) XIAFLEX-treated patients in clinical studies. In other XIAFLEX-treated patients (9 of 1044; 0.9%), a diagnosis of corporal rupture cannot be excluded. Severe penile hematoma was also reported as an adverse reaction in 39 of 1044 (3.7%) XIAFLEX-treated patients. (5.2)
- XIAFLEX is available for the treatment of Peyronie’s disease only through a restricted program called the XIAFLEX REMS Program. (5.3)

1 INDICATIONS AND USAGE

XIAFLEX is a combination of bacterial collagenases indicated for:

- The treatment of adult patients with Dupuytren’s contracture with a palpable cord (1)
- The treatment of adult men with Peyronie’s disease with a palpable plaque and curvature deformity of at least 30 degrees at the start of therapy (1)

2 DOSAGE AND ADMINISTRATION

Dupuytren’s Contracture (2.1)

- XIAFLEX should be administered by a healthcare provider experienced in injection procedures of the hand and in the treatment of Dupuytren’s contracture.
- Reconstitute XIAFLEX lyophilized powder with only the supplied diluent prior to use.
- Inject 0.58 mg of XIAFLEX into each palpable Dupuytren’s cord with a contracture of a metacarpophalangeal (MP) joint or a proximal interphalangeal (PIP) joint according to the injection procedure.
- Up to two joints in the same hand may be treated during a treatment visit. (2.1)
- Approximately 24 to 72 hours following an injection, perform a finger extension procedure if a contracture persists.
- Injections and finger extension procedures may be administered up to 3 times per cord at approximately 4-week intervals.
- Inject up to two cords in the same hand at a treatment visit. If a patient has other cords with contractures, inject those cords at another treatment visit.

Peyronie’s Disease (2.2)

- XIAFLEX should be administered by a healthcare provider experienced in the treatment of male urological diseases.
- Reconstitute XIAFLEX lyophilized powder with only the supplied diluent prior to use.
- A treatment cycle consists of two XIAFLEX injection procedures and a penile modeling procedure.
- Induce a penile erection. A single intracavernosal injection of 10 or 20 mcg of alprostadil may be used for this purpose.
- With the penis in the erect state, identify and mark the target area in the Peyronie’s plaque to be injected.
- The penis should be in a flaccid state before injecting XIAFLEX.
- Inject 0.58 mg XIAFLEX into the target plaque once on each of 2 days, 1 to 3 days apart, according to the injection procedure.
- Perform a penile modeling procedure 1 to 3 days after the second injection of each treatment cycle.
- For each plaque causing the curvature deformity, up to 4 treatment cycles may be administered. Each treatment cycle may be repeated at approximately 6-week intervals. If the curvature deformity is less than 15 degrees after the first, second or third treatment cycle, or if further treatment is not clinically indicated, then subsequent treatment cycles should not be administered.

3 DOSAGE FORMS AND STRENGTHS

Single-use glass vials containing 0.9 mg of collagenase clostridium histolyticum as a sterile, lyophilized powder for reconstitution. Sterile diluent for reconstitution is also provided in a single-use glass vial. (3)

4 CONTRAINDICATIONS

- Peyronie’s plaques that involve the penile urethra (4)
- History of hypersensitivity to XIAFLEX or to collagenase used in other therapeutic applications (4)

5 WARNINGS AND PRECAUTIONS

- Tendon rupture or serious injury to the injected finger/hand: Avoid injecting XIAFLEX into tendons, nerves, blood vessels, or other collagen-containing structure of the hand. Injection into these structures may result in possible permanent injury, such as tendon rupture, ligament damage, or skin laceration. (5.1)
- Corporal rupture (penile fracture) or other serious injury to the penis: Avoid injecting into the urethra, nerves, blood vessels, corpora cavernosa or other collagen-containing structures of the penis. Injection into these structures may result in possible permanent injury such as corporal rupture (penile fracture). (5.2)
- Hypersensitivity reactions, including anaphylaxis: Healthcare providers should be prepared to address hypersensitivity reactions, including anaphylaxis, following XIAFLEX injections. (5.4)
- Patients with abnormal coagulation: Use with caution, including in patients who have received anticoagulant medications other than low-dose aspirin within 7 days of the injection. (5.5)
- Acute post-injection back pain reactions: Observe patients and provide palliative support as needed. Administer the smallest number of treatment cycles necessary to treat the patient’s curvature deformity (5.6, 6.4)
- Syncope and presyncope: Make patients aware that post-injection pain can trigger syncope and presyncope. If presyncope occurs, patients should remain recumbent until symptoms resolve. (5.7, 6.4)

6 ADVERSE REACTIONS

Dupuytren’s Contracture (6.1)

The most common adverse reactions reported in ≥ 25% of patients treated with XIAFLEX and at an incidence greater than placebo were edema peripheral (e.g., swelling of the injected hand), contusion, injection site hemorrhage, injection site reaction, and pain in the injected extremity.

Peyronie’s Disease (6.2)

The most frequently reported adverse drug reactions reported with ≥ 25% of patients treated with XIAFLEX and at an incidence greater than placebo were penile hematoma, penile swelling and penile pain.

To report SUSPECTED ADVERSE REACTIONS, contact Endo at 1-800-462-3636 or FDA at 1-800-FDA-1088 or www.fda.gov/medwatch.

FULL PRESCRIBING INFORMATION

WARNING: CORPORAL RUPTURE (PENILE FRACTURE) OR OTHER SERIOUS PENILE INJURY IN THE TREATMENT OF PEYRONIE’S DISEASE

Corporal rupture (penile fracture) was reported as an adverse reaction in 5 of 1044 (0.5%) XIAFLEX-treated patients in clinical studies. In other XIAFLEX-treated patients (9 of 1044; 0.9%), a combination of penile ecchymoses or hematoma, sudden penile detumescence, and/or a penile “popping” sound or sensation was reported, and in these cases, a diagnosis of corporal rupture cannot be excluded. Severe penile hematoma was also reported as an adverse reaction in 39 of 1044 (3.7%) XIAFLEX-treated patients [see Warnings and Precautions (5.2)].

Signs or symptoms that may reflect serious penile injury should be promptly evaluated to assess for corporal rupture or severe penile hematoma which may require surgical intervention [see Warnings and Precautions (5.2)].

Because of the risks of corporal rupture or other serious penile injury, XIAFLEX is available for the treatment of Peyronie’s disease only through a restricted program under a Risk Evaluation and Mitigation Strategy (REMS) called the XIAFLEX REMS Program [see Warnings and Precautions (5.3)].

1 INDICATIONS AND USAGE

XIAFLEX is indicated for the treatment of adult patients with Dupuytren’s contracture with a palpable cord.

XIAFLEX is indicated for the treatment of adult men with Peyronie’s disease with a palpable plaque and curvature deformity of at least 30 degrees at the start of therapy.

2 DOSAGE AND ADMINISTRATION

2.1 Dosage and Administration for Dupuytren’s Contracture

Dosing Overview for Dupuytren’s Contracture

XIAFLEX should be administered by a healthcare provider experienced in injection procedures of the hand and in the treatment of patients with Dupuytren’s contracture.

XIAFLEX, supplied as a lyophilized powder, must be reconstituted with the provided diluent prior to use [see Dosage and Administration (2.1)]. The dose of XIAFLEX is 0.58 mg per injection into a palpable cord with a contracture of a metacarpophalangeal (MP) joint or a proximal interphalangeal (PIP) joint [see Dosage and Administration (2.1)]. Each vial of XIAFLEX and sterile diluent should only be used for a single injection. If two joints on the same hand are to be treated during a treatment visit, separate vials and syringes should be used for each reconstitution and injection.

Table 1 displays an overview of the volumes of sterile diluent for reconstitution and the reconstituted XIAFLEX solution to be used in the intralesional injection [see Dosage and Administration (2.1)]. Approximately 24 to 72 hours after injection, perform a finger extension procedure if a contracture persists to facilitate cord disruption [see Dosage and Administration (2.1)].

Table 1. Volumes Needed for Reconstitution and Administration for Dupuytren’s Contracture
 | For cords affecting MP joints | For cords affecting PIP joints
Sterile Diluent for Reconstitution
Volume | 0.39 mL | 0.31 mL
Reconstituted XIAFLEX Solution to be Injected^1
Volume | 0.25 mL | 0.20 mL
^1 The reconstituted XIAFLEX solution to be used in the intralesional injection contains 0.58 mg of XIAFLEX.
Note: The entire reconstituted XIAFLEX solution contains 0.9 mg of XIAFLEX.
Reconstituted XIAFLEX solution remaining in the vial after the injection should be discarded.

Four weeks after the XIAFLEX injection and finger extension procedure, if a MP or PIP contracture remains, the cord may be re-injected with a single dose of 0.58 mg of XIAFLEX and the finger extension procedure may be repeated (approximately 24 to 72 hours after injection). Injections and finger extension procedures may be administered up to 3 times per cord at approximately 4-week intervals.

Perform up to two injections in the same hand according to the injection procedure during a treatment visit. Two palpable cords affecting two joints may be injected or one palpable cord affecting two joints in the same finger may be injected at two locations during a treatment visit. If patient has other palpable cords with contractures of MP or PIP joints, these cords may be injected with XIAFLEX at other treatment visits approximately 4 weeks apart.

Reconstitution of the Lyophilized Powder for Dupuytren’s Contracture

a) Before use, remove the vial(s) containing the lyophilized powder of XIAFLEX and the vial(s) containing the diluent for reconstitution from the refrigerator and allow the vials to stand at room temperature for at least 15 minutes and no longer than 60 minutes. Visually inspect the vial(s) containing XIAFLEX. The cake of lyophilized powder should be intact and white in color.

b) After removal of the flip-off cap from each vial, using aseptic technique swab the rubber stopper and surrounding surface of the vial(s) containing XIAFLEX and the vial(s) containing the diluent for reconstitution with sterile alcohol (no other antiseptics should be used).

c) Use only the supplied diluent for reconstitution. The diluent contains calcium which is required for the activity of XIAFLEX.

d) Using a 1-mL syringe that contains 0.01-mL graduations with a 27-gauge 1/2-inch needle (not supplied), withdraw a volume of the diluent supplied, as follows:

- 0.39 mL for cords affecting a MP joint or
- 0.31 mL for cords affecting a PIP joint.

e) Inject the diluent slowly into the sides of the vial containing the lyophilized powder of XIAFLEX. Do not invert the vial or shake the solution. Slowly swirl the solution to ensure that all of the lyophilized powder has gone into solution. If administering two injections in the same hand during a treatment visit, use a new syringe to reconstitute a second vial of XIAFLEX with a second vial of diluent.

f) The reconstituted XIAFLEX solution can be kept at room temperature (20°C to 25°C/68°F to 77°F) for up to 1 hour or refrigerated at 2°C to 8°C (36°F to 46°F) for up to 4 hours prior to administration. If the reconstituted XIAFLEX solution is refrigerated, allow this solution to return to room temperature for approximately 15 minutes before use.

g) Discard the syringe(s) and needle(s) used for reconstitution and the diluent vial(s).

Preparation Prior to Injection for Dupuytren’s Contracture

a) The reconstituted XIAFLEX solution should be clear. Inspect the solution visually for particulate matter and discoloration prior to administration. If the solution contains particulates, is cloudy, or is discolored, do not inject the reconstituted solution.

b) Administration of a local anesthetic agent prior to injection is not recommended, as it may interfere with proper placement of the XIAFLEX injection.

c) If injecting into a cord affecting the PIP joint of the fifth finger, care should be taken to inject as close to the palmar digital crease as possible (as far proximal to the digital PIP joint crease), and the needle insertion should not be more than 2 to 3 mm in depth. Tendon ruptures occurred after XIAFLEX injections near the digital PIP joint crease [see Warnings and Precautions (5.1)].

d) Reconfirm the cord(s) to be injected. The site chosen for each injection should be the area where the contracting cord is maximally separated from the underlying flexor tendons and where the skin is not intimately adhered to the cord.

e) Apply an antiseptic at the site(s) of the injection(s) and allow the skin to dry.

Injection Procedure for Dupuytren’s Contracture

a) Using a new 1-mL hubless syringe that contains 0.01-mL graduations with a permanently fixed, 27-gauge 1/2-inch needle (not supplied), withdraw a volume of reconstituted solution (containing 0.58 mg of XIAFLEX) as follows:

- 0.25 mL for cords affecting a MP joint or
- 0.20 mL for cords affecting a PIP joint.

b) With your non-dominant hand, secure the patient’s hand to be treated while simultaneously applying tension to the cord. With your dominant hand, place the needle into the cord, using caution to keep the needle within the cord. Avoid having the needle tip pass completely through the cord to help minimize the potential for injection of XIAFLEX into tissues other than the cord [see Warnings and Precautions (5.1)]. After needle placement, if there is any concern that the needle is in the flexor tendon, apply a small amount of passive motion at the distal interphalangeal (DIP) joint. If insertion of the needle into a tendon is suspected or paresthesia is noted by the patient, withdraw the needle and reposition it into the cord.

c) If the needle is in the proper location, there will be some resistance noted during the injection procedure. After confirming that the needle is correctly placed in the cord, inject approximately one-third of the dose.

d) Next, withdraw the needle tip from the cord and reposition it in a slightly more distal location (approximately 2 to 3 mm) to the initial injection in the cord and inject another one-third of the dose.

e) Again withdraw the needle tip from the cord and reposition it a third time proximal to the initial injection (approximately 2 to 3 mm) and inject the final portion of the dose into the cord.

f) When administering two injections in the same hand during a treatment visit, use a new syringe and separate vial of reconstituted solution for each injection. Repeat steps a through f.

g) When administering two injections in the same hand during a treatment visit, begin with the affected finger in the most medial aspect of the hand and continue toward the lateral aspect (eg, fifth finger to index finger). When administering two injections in a cord affecting two joints in the same finger, begin with the affected joint in the most proximal aspect of the finger and continue toward the distal aspect (eg, MP to PIP).

h) Wrap the patient’s treated hand with a soft, bulky, gauze dressing.

i) Instruct the patient to limit motion of the treated finger(s) and to keep the injected hand elevated until bedtime.

j) Instruct the patient not to attempt to disrupt the injected cord(s) by self-manipulation and to return to the healthcare provider’s office the next day for follow-up and a finger extension procedure(s), if needed.

k) Discard the unused portion of the reconstituted solution and diluent after injection. Do not store, pool, or use any vials containing unused reconstituted solution or diluent.

Finger Extension Procedure for Dupuytren’s Contracture

a) At the follow-up visit approximately 24 to 72 hours after the injection(s), if a contracture remains, perform a passive finger extension procedure on each treated joint (as described below) to facilitate cord disruption. If two joints in one finger were treated, perform the finger extension procedure on the affected MP joint before performing the finger extension procedure on the affected PIP joint.

b) Local anesthesia may be used. Avoid direct pressure on the injection site as it will likely be tender. Care should be taken during release of contracture, as some patients may experience skin splitting. If this occurs, cover the area with gauze and apply gentle pressure until bleeding stops. Standard wound care with regular dressings should be applied.

c) While the patient’s wrist is in the flexed position, apply moderate stretching pressure to the injected cord by extending the finger for approximately 10 to 20 seconds. For cords affecting the PIP joint, perform the finger extension procedure when the MP joint is in the flexed position.

d) If the first finger extension procedure does not result in disruption of the cord, a second and third attempt can be performed at 5- to 10-minute intervals. However, no more than 3 attempts per joint are recommended to disrupt a cord.

e) If the cord has not been disrupted after 3 attempts, a follow-up visit may be scheduled in approximately 4 weeks. If, at that subsequent visit, the contracted cord persists, an additional XIAFLEX injection with finger extension procedures may be performed [see Dosage and Administration (2.1)].

f) Following the finger extension procedure(s), fit patient with a splint and provide instructions for use at bedtime for up to 4 months to maintain finger extension. Also, instruct the patient to perform finger extension and flexion exercises several times a day for several months.

2.2 Dosage and Administration for Peyronie’s Disease

Dosing Overview for Peyronie's Disease

XIAFLEX should be administered by a healthcare provider experienced in the treatment of male urological diseases, who has completed required training for use of XIAFLEX in the treatment of Peyronie’s disease.

XIAFLEX, supplied as lyophilized powder, must be reconstituted with the provided diluent prior to use [see Dosage and Administration (2.2)]. The dose of XIAFLEX is 0.58 mg per injection administered into a Peyronie’s plaque. If more than one plaque is present, inject into the plaque causing the curvature deformity.

A treatment course consists of a maximum of 4 treatment cycles. Each treatment cycle consists of two XIAFLEX injection procedures [see Dosage and Administration (2.2)] and one penile modeling procedure [see Dosage and Administration (2.2)]. The second XIAFLEX injection procedure is performed 1 to 3 days after the first. The penile modeling procedure is performed 1 to 3 days after the second injection of the treatment cycle. The interval between treatment cycles is approximately 6 weeks. The treatment course therefore, consists of a maximum of 8 injection procedures and 4 modeling procedures.

If the curvature deformity is less than 15 degrees after the first, second or third treatment cycle, or if the healthcare provider determines that further treatment is not clinically indicated, then the subsequent treatment cycles should not be administered.

The safety of more than one treatment course of XIAFLEX is not known.

Table 2 displays an overview of the volume of sterile diluent for reconstitution and the reconstituted XIAFLEX solution to be used in the intralesional injection [see Dosage and Administration (2.2)].

Table 2. Volumes Needed for Reconstitution and Administration
Sterile Diluent for Reconstitution
Volume | 0.39 mL
Reconstituted XIAFLEX Solution to be Injected^1
Volume | 0.25 mL
^1 The reconstituted XIAFLEX solution to be used in the intralesional injection contains 0.58 mg of XIAFLEX.
Note: The entire reconstituted XIAFLEX solution contains 0.9 mg of XIAFLEX.
Reconstituted XIAFLEX solution remaining in the vial after the injection should be discarded.

Reconstitution of the Lyophilized Powder for Peyronie’s Disease

a) Before use, remove the vial containing the lyophilized powder of XIAFLEX and the vial containing the diluent for reconstitution from the refrigerator and allow the 2 vials to stand at room temperature for at least 15 minutes and no longer than 60 minutes. Visually inspect the vial containing XIAFLEX. The cake of lyophilized powder should be intact and white in color.

b) After removal of the flip-off cap from each vial, using aseptic technique swab the rubber stopper and surrounding surface of the vial containing XIAFLEX and the vial containing the diluent for reconstitution with sterile alcohol (no other antiseptics should be used).

c) Use only the supplied diluent for reconstitution. The diluent contains calcium which is required for the activity of XIAFLEX.

d) Using a 1-mL syringe with 0.01-mL graduations with a 27-gauge 1/2-inch needle (not supplied), withdraw a volume of 0.39 mL of the diluent supplied.

e) Inject the diluent slowly into the sides of the vial containing the lyophilized powder of XIAFLEX. Do not invert the vial or shake the solution. Slowly swirl the solution to ensure that all of the lyophilized powder has gone into solution.

f) The reconstituted XIAFLEX solution can be kept at room temperature (20°C to 25°C/68°F to 77°F) for up to 1 hour or refrigerated at 2°C to 8°C (36°F to 46°F) for up to 4 hours prior to administration. If the reconstituted XIAFLEX solution is refrigerated, allow this solution to return to room temperature for approximately 15 minutes before use.

g) Discard the syringe and needle used for reconstitution and the diluent vial.

Identification of Treatment Area for Peyronie’s Disease

a) Prior to each treatment cycle, identify the treatment area as follows:

- Induce a penile erection. A single intracavernosal injection of 10 or 20 mcg of alprostadil may be used for this purpose. Apply antiseptic at the site of the injection and allow the skin to dry prior to the intracavernosal injection.
- Locate the plaque at the point of maximum concavity (or focal point) in the bend of the penis.
- Mark the point with a surgical marker. This indicates the target area in the plaque for XIAFLEX deposition.

Injection Procedure for Peyronie’s Disease

a) The reconstituted XIAFLEX solution should be clear. Inspect the solution visually for particulate matter and discoloration prior to administration. If the solution contains particulates, is cloudy, or is discolored, do not inject the reconstituted solution.

b) Apply antiseptic at the site of the injection and allow the skin to dry.

c) Administer suitable local anesthetic, if desired.

d) Using a new hubless syringe containing 0.01-mL graduations with a permanently fixed 27-gauge 1/2-inch needle (not supplied), withdraw a volume of 0.25 mL of reconstituted solution (containing 0.58 mg of XIAFLEX).

e) The penis should be in a flaccid state before XIAFLEX is injected. Place the needle tip on the side of the target plaque in alignment with the point of maximal concavity. Orient the needle so that it enters the edge of the plaque and advance the needle into the plaque itself from the side. Do not advance the needle beneath the plaque nor perpendicularly towards the corpora cavernosum.

f) Insert and advance the needle transversely through the width of the plaque, towards the opposite side of the plaque without passing completely through it. Proper needle position is tested and confirmed by carefully noting resistance to minimal depression of the syringe plunger.

g) With the tip of the needle placed within the plaque, initiate injection, maintaining steady pressure to slowly inject XIAFLEX into the plaque. Withdraw the needle slowly so as to deposit the full dose along the needle track within the plaque. For plaques that are only a few millimeters in width, the distance of withdrawal of the syringe may be very minimal. The goal is always to deposit the full dose entirely within the plaque.

h) Upon complete withdrawal of the needle, apply gentle pressure at the injection site. Apply a dressing as necessary.

i) Discard the unused portion of the reconstituted solution and diluent after each injection. Do not store, pool, or use any vials containing unused reconstituted solution or diluent.

j) The second injection of each treatment cycle should be made approximately 2 to 3 mm apart from the first injection.

Penile Modeling Procedure for Peyronie’s Disease

Penile modeling helps relieve curvature deformity and straighten the penile shaft. At a follow-up visit 1 to 3 days after the second injection of each treatment cycle, perform a penile modeling procedure (as described below) on the flaccid penis to stretch and elongate the treated plaque:

- Administer suitable local anesthetic, if desired.
- Wearing gloves, grasp the plaque or indurated portion of the flaccid penis about 1 cm proximal and distal to the injection site. Avoid direct pressure on the injection site.
- Using the target plaque as a fulcrum point, use both hands to apply firm, steady pressure to elongate and stretch the plaque. The goal is to gradually create bending opposite to the patient’s penile curvature, with stretching to the point of moderate resistance. Hold pressure for 30 seconds then release.
- After a 30 second rest period, repeat the penile modeling technique for a total of 3 modeling attempts at 30 seconds for each attempt.

In addition to the in-office penile modeling procedure, patients should be instructed to self-perform penile modeling activities at home each day for the 6-week period following the investigator penile plaque modeling visit of each treatment cycle as follows:

- During spontaneous erections, gently attempt to straighten the penis without producing pain and hold the penis in a straightened position for 30 seconds.
- The flaccid penis should be gently stretched three times daily. Slow, gentle force should be used without producing pain.

3 DOSAGE FORMS AND STRENGTHS

XIAFLEX is supplied in single-use glass vials containing 0.9 mg of collagenase clostridium histolyticum as a sterile, lyophilized powder for reconstitution. Sterile diluent for reconstitution is provided in the package in a single-use glass vial containing 3 mL of 0.3 mg/mL calcium chloride dihydrate in 0.9% sodium chloride.

4 CONTRAINDICATIONS

XIAFLEX is contraindicated in:

- the treatment of Peyronie’s plaques that involve the penile urethra due to potential risk to this structure.
- patients with a history of hypersensitivity to XIAFLEX or to collagenase used in any other therapeutic application or application method [see Warnings and Precautions (5.4)].

5 WARNINGS AND PRECAUTIONS

5.1 Tendon Rupture or Other Serious Injury to the Injected Finger/Hand in the Treatment of Dupuytren’s Contracture

In the controlled and uncontrolled portions of clinical trials in Dupuytren’s contracture, flexor tendon ruptures occurred after XIAFLEX injection [see Adverse Reactions (6.1)]. Injection of XIAFLEX into collagen-containing structures such as tendons or ligaments of the hand may result in damage to those structures and possible permanent injury such as tendon rupture or ligament damage. Therefore, XIAFLEX should be injected only into the collagen cord with a MP or PIP joint contracture, and care should be taken to avoid injecting into tendons, nerves, blood vessels, or other collagen-containing structures of the hand. When injecting a cord affecting a PIP joint of the fifth finger, the needle insertion should not be more than 2 to 3 mm in depth and avoid injecting more than 4 mm distal to the palmar digital crease [see Dosage and Administration (2.1)].

Other XIAFLEX-associated serious local adverse reactions included pulley rupture, ligament injury, complex regional pain syndrome (CRPS), sensory abnormality of the hand, and skin laceration (tear). In a historically controlled post-marketing trial, the incidence of skin laceration (22%) was higher for subjects treated with two concurrent injections of XIAFLEX compared with subjects treated with up to three single injections in the placebo-controlled premarketing trials (9%). Postmarketing cases of skin laceration requiring skin graft after finger extension procedures and local skin and soft-tissue necrosis, some requiring skin grafting or, other surgical interventions including finger amputation have been reported. Signs or symptoms that may reflect serious injury to the injected finger/hand should be promptly evaluated because surgical intervention may be required.

5.2 Corporal Rupture (Penile Fracture) or Other Serious Injury to the Penis in the Treatment of Peyronie’s Disease

Corporal rupture was reported as an adverse reaction after XIAFLEX injections in 5 of 1044 (0.5%) XIAFLEX-treated patients in the controlled and uncontrolled clinical trials in Peyronie’s disease.

In other XIAFLEX-treated patients (9 of 1044; 0.9%), a combination of penile ecchymoses or hematoma, sudden penile detumescence, and/or a penile “popping” sound or sensation was reported, and in these cases, a diagnosis of corporal rupture cannot be excluded. These patients were managed without surgical intervention, but the long-term consequences are unknown.

Severe penile hematoma was also reported as an adverse reaction in 39 of 1044 patients (3.7%) in the controlled and uncontrolled clinical trials in Peyronie’s disease [see Adverse Reactions (6)].

In the postmarketing setting, cases of localized skin and soft tissue necrosis occurring as sequelae of penile hematoma have been reported. Some of the cases required surgical intervention.

Injection of XIAFLEX into collagen-containing structures such as the corpora cavernosa of the penis may result in damage to those structures and possible injury such as corporal rupture (penile fracture). Therefore, XIAFLEX should be injected only into the Peyronie’s plaque and care should be taken to avoid injecting into the urethra, nerves, blood vessels, corpora cavernosa or other collagen-containing structures of the penis.

Signs or symptoms that may reflect serious injury to the penis should be promptly evaluated in order to assess for corporal rupture or severe penile hematoma, which may require surgical intervention.

5.3 XIAFLEX REMS Program

Because of the risks of corporal rupture (penile fracture) or other serious penile injury in the treatment of Peyronie’s disease, XIAFLEX is available only through the XIAFLEX REMS Program [see Warnings and Precautions (5.2)].

Required components of the XIAFLEX REMS Program include the following:

- Prescribers must be certified with the program by enrolling and completing training in the administration of XIAFLEX treatment for Peyronie’s disease.
- Healthcare sites must be certified with the program and ensure that XIAFLEX is only dispensed for use by certified prescribers.

Further information is available at www.XIAFLEXREMS.com or 1-877-313-1235.

5.4 Hypersensitivity Reactions, Including Anaphylaxis

In the controlled portions of the clinical trials in Dupuytren’s contracture (Studies 1 and 2), a greater proportion of XIAFLEX-treated patients (15%) compared to placebo-treated patients (1%) had mild allergic reactions (pruritus) after up to 3 injections. The incidence of XIAFLEX-associated pruritus increased after more XIAFLEX injections in patients with Dupuytren’s contracture.

In the double-blind, placebo-controlled portions of the clinical trials in Peyronie’s disease (Studies 1 and 2), a greater proportion of XIAFLEX-treated patients (4%) compared to placebo-treated patients (1%) had localized pruritus after up to 4 treatment cycles (involving up to 8 XIAFLEX injection procedures). The incidence of XIAFLEX-associated pruritus was similar after each injection regardless of the number of injections administered.

Because XIAFLEX contains foreign proteins, severe allergic reactions to XIAFLEX can occur. Anaphylaxis was reported in a post-marketing clinical trial (Study 3) in one patient who had previous exposure to XIAFLEX for the treatment of Dupuytren’s contracture. Some patients with Dupuytren’s contracture developed IgE-anti-drug antibodies in greater proportions and higher titers with successive XIAFLEX injections. Healthcare providers should be prepared to address severe allergic reactions following XIAFLEX injections.

5.5 Risk of Bleeding in Patients with Abnormal Coagulation

In the XIAFLEX trials in Dupuytren’s contracture (Studies 1 and 2), 70% and 38% of XIAFLEX-treated patients developed an ecchymosis/contusion or an injection site hemorrhage, respectively (see Table 3). In the XIAFLEX controlled trials in Peyronie’s disease (Studies 1 and 2), 65.5% of XIAFLEX-treated patients developed penile hematoma, and 14.5% developed penile ecchymosis (see Table 5). Patients with abnormal coagulation (except for patients taking low-dose aspirin, e.g., up to 150 mg per day) were excluded from participating in these studies.

Therefore, the efficacy and safety of XIAFLEX in patients receiving anticoagulant medications (other than low-dose aspirin, e.g., up to 150 mg per day) within 7 days prior to XIAFLEX administration is not known. In addition, it is recommended to avoid use of XIAFLEX in patients with coagulation disorders, including patients receiving concomitant anticoagulants (except for low-dose aspirin).

5.6 Acute Post-Injection Back Pain Reactions

Acute post-injection back pain reactions have been reported in the postmarketing period in patients treated with XIAFLEX for Peyronie’s disease [see Adverse Reactions (6.4)]. These events typically have an onset immediately or within minutes of injection. The acute lower back pain can be mild to severe in intensity and can radiate to the legs, arms and chest. Other systemic symptoms, such as chest pain, headache, and dyspnea, have been reported along with back pain episodes. None of the events were reported to occur after the patient’s first XIAFLEX injection and a few were reported to occur during a second treatment course [see Dosage and Administration (2.2)]. Reported events typically resolved within 15 minutes, but some lasted up to 30 minutes, and one event lasted 1.5 hours. Reported events typically did not require intervention, but some required observation and treatment with analgesics.

5.7 Syncope and Presyncope

Cases of syncope and presyncope have been reported in the postmarketing period in patients treated with XIAFLEX.

Most, but not all, cases in patients with Peyronie's disease, occurred in association with post-injection penile pain and hematoma, penile pain with spontaneous erections, and pain during micturition. These potential triggers for the syncopal events suggest a vasovagal mechanism. Make Peyronie's disease patients aware of the potential for penile pain and painful penile hematoma that could trigger syncope and presyncope after treatment with XIAFLEX.

In most cases in patients with Dupuytren's Contracture, the injection procedure, finger extension procedure, or pain following the procedures were reported as potential triggers for the events, suggesting a vasovagal mechanism. Most, but not all cases in patients with Dupuytren's contracture, occurred in the immediate treatment period (injection or finger extension procedure) or within 1 to 2 days following the injection or finger extension procedure.

If presyncopal symptoms occur, patients should remain recumbent until symptoms resolve. Syncope may be associated with bodily injuries, including concussion, head abrasion, and other accidental injuries.

6 ADVERSE REACTIONS

The following serious adverse reactions in patients with Dupuytren’s contracture are discussed in greater detail elsewhere in the labeling:

- Tendon ruptures or other serious injury to the injected extremity [see Warnings and Precautions (5.1)]

The following serious adverse reactions in patients with Peyronie’s disease are discussed in greater detail elsewhere in the labeling:

- Corporal rupture (penile fracture) and severe penile hematoma [see Warnings and Precautions (5.2)]
- In other XIAFLEX-treated patients, a combination of penile ecchymoses or hematoma, sudden penile detumescence, and/or a penile “popping” sound or sensation was reported, and in these cases, a diagnosis of corporal rupture cannot be excluded [see Warnings and Precautions (5.2)]

6.1 Clinical Studies Experience in Patients with Dupuytren’s Contracture

Because clinical studies are conducted under widely varying conditions, adverse reaction rates observed in the clinical studies of a drug cannot be directly compared to rates in the clinical studies of another drug and may not reflect the rates observed in practice.

Out of 1082 patients who received 0.58 mg of XIAFLEX in the controlled and uncontrolled portions of the XIAFLEX studies (2630 XIAFLEX injections), 3 (0.3%) patients had a flexor tendon rupture of the treated finger within 7 days of the injection.

The data described below are based on two pooled randomized, double-blind, placebo-controlled trials through Day 90 in patients with Dupuytren’s contracture (Studies 1 and 2). In these trials, patients were treated with up to 3 injections of 0.58 mg of XIAFLEX or placebo with approximately 4-week intervals between injections and the patients had finger extension procedures the day after injection, if needed, to facilitate disruption of the cord [see Clinical Studies (14)]. These trials were comprised of 374 patients of whom 249 and 125 received 0.58 mg of XIAFLEX and placebo, respectively. The mean age was 63 years, 80% were male and 20% were female, and 100% were white.

In the placebo-controlled portions of Studies 1 and 2 through Day 90, 98% and 51% of XIAFLEX-treated and placebo-treated patients had an adverse reaction after up to 3 injections, respectively. Over 95% of XIAFLEX-treated patients had an adverse reaction of the injected extremity after up to 3 injections. Approximately 81% of these local reactions resolved without intervention within 4 weeks of XIAFLEX injections. The adverse reaction profile was similar for each injection, regardless of the number of injections administered. However, the incidence of pruritus increased with more injections [see Warnings and Precautions (5.4)].

The most frequently reported adverse drug reactions (≥ 25%) in the XIAFLEX clinical trials in patients with Dupuytren’s contracture included edema peripheral (mostly swelling of the injected hand), contusion, injection site hemorrhage, injection site reaction, and pain in the treated extremity. Table 3 shows the incidence of adverse reactions that were reported in greater than or equal to 5% of XIAFLEX-treated patients and at a frequency greater than placebo-treated patients after up to 3 injections in the pooled placebo-controlled trials through Day 90 (Studies 1 and 2).

Table 3. Adverse Reactions Occurring in ≥ 5% of XIAFLEX-Treated Patients with Dupuytren’s Contracture and at a Greater Incidence than Placebo in the Placebo-Controlled Trials Through Day 90 After Up to 3 Injections
Adverse Reaction | XIAFLEX N=249 | Placebo N=125
All Adverse Reactions | 98% | 51%
Edema peripherala | 73% | 5%
Contusionb | 70% | 3%
Injection site hemorrhage | 38% | 3%
Injection site reactionc | 35% | 6%
Pain in extremity | 35% | 4%
Tenderness | 24% | 0%
Injection site swellingd | 24% | 6%
Prurituse | 15% | 1%
Lymphadenopathyf | 13% | 0%
Skin laceration | 9% | 0%
Lymph node pain | 8% | 0%
Erythema | 6% | 0%
Axillary pain | 6% | 0%
a Most of these events were swelling of the injected hand.
b Includes the terms: contusion (any body system) and ecchymosis.
c Includes the terms: injection site reaction, injection site erythema, injection site inflammation, injection site irritation, injection site pain, and injection site warmth.
d Includes the terms: injection site swelling and injection site edema.
e Includes the terms: pruritus and injection site pruritus.
f Includes the terms: lymphadenopathy and axillary mass.

Some patients developed vasovagal syncope after finger extension procedures.

The safety of two concurrent injections of XIAFLEX 0.58 mg into Dupuytren’s cords in the same hand was evaluated in a historically-controlled, open-label multi-center trial in 715 adult subjects with Dupuytren’s contracture (Study 3). In Study 3, finger extension procedures were performed approximately 24 to 72 hours after injection. The patient demographics were similar to Studies 1 and 2.

Out of 715 patients who received two concurrent injections of XIAFLEX 0.58 mg in the same hand (1450 XIAFLEX injections) in Study 3, one (0.1%) patient experienced a tendon rupture of the treated finger within 3 days of the injection.

Table 4 shows the incidence of adverse reactions that were reported in greater than or equal to 5% of XIAFLEX-treated patients after two concurrent injections of XIAFLEX in the same hand through Day 60 in Study 3.

Table 4. Adverse Reactions Occurring in ≥5.0% of Subjects Who Received Two Concurrent Injections of XIAFLEX in Study 3
Adverse Reaction | XIAFLEX N=715
Subjects with ≥1 adverse reaction | 95%
Edema peripheral | 77%
Contusion | 59%
Pain in extremity | 51%
Laceration | 22%
Pruritus | 15%
Injection site pain | 14%
Lymphadenopathy | 13%
Blood blister | 12%
Injection site hematoma | 8%
Axillary pain | 7%
Injection site hemorrhage | 6%
Injection site swelling | 5%
Ecchymosis | 5%

Safety of Retreatment of Recurrent Contractures

An observational, open-label study was conducted in subjects who had participated in XIAFLEX clinical trials for Dupuytren’s contracture (Study 4). A subset of patients who had recurrence of contracture in a joint that was previously successfully treated with XIAFLEX in Study 4 were retreated (Study 5). No new safety signals were identified among subjects who were retreated with XIAFLEX.

6.2 Clinical Studies Experience in Patients with Peyronie’s Disease

Because clinical studies are conducted under widely varying conditions, adverse reaction rates observed in the clinical studies of a drug cannot be directly compared to rates in the clinical studies of another drug and may not reflect the rates observed in practice.

In the controlled and uncontrolled clinical studies of XIAFLEX in Peyronie’s disease, 1044 patients received a total of 7466 XIAFLEX injections.

Corporal Rupture and Other Serious Penile Injury

- Corporal rupture was reported as an adverse reaction after XIAFLEX injections in 5 of 1044 (0.5%) XIAFLEX treated patients.
- In other XIAFLEX-treated patients (9 of 1044; 0.9%), a combination of penile ecchymoses or hematoma, sudden penile detumescence, and/or a penile “popping” sound or sensation was reported, and in these cases, a diagnosis of corporal rupture cannot be excluded. These patients were managed without surgical intervention, but the long-term consequences are unknown.
- Severe penile hematoma was also reported as an adverse reaction in 39 of 1044 patients (3.7%) in the controlled and uncontrolled clinical trials in Peyronie’s disease [see Adverse Reactions (6)].

The data described below are based on two identical, pooled, randomized, double-blind, placebo-controlled, multicenter trials through Day 365 in patients with Peyronie’s disease (Studies 1 and 2). These trials included 832 patients of whom 551 and 281 received XIAFLEX and placebo, respectively. In these trials, patients were given up to 4 treatment cycles of XIAFLEX or placebo. In each cycle, two injections of XIAFLEX or two injections of placebo were administered 1 to 3 days apart. A penile modeling procedure was performed at the study site on patients 1 to 3 days after the second injection of the cycle. The treatment cycle was repeated at approximately 6-week intervals up to 3 additional times, for a maximum of 8 total injection procedures and 4 total modeling procedures [see Clinical Studies (14.2)].

The majority of Peyronie’s patients experienced at least one adverse reaction (92% XIAFLEX-treated patients, 61% placebo-treated). Most adverse reactions were local events of the penis and groin and the majority of these events were of mild or moderate severity, and most (79%) resolved within 14 days of the injection. The adverse reaction profile was similar after each injection, regardless of the number of injections administered.

The most frequently reported adverse drug reactions (≥ 25%) in the XIAFLEX clinical trials in patients with Peyronie’s disease were penile hematoma, penile swelling, and penile pain. Table 5 shows the incidence of adverse reactions that were reported in greater than or equal to 1% of XIAFLEX-treated patients and at a frequency greater than placebo-treated patients after up to 8 injections in the pooled placebo-controlled trials through Day 365.

Table 5. Adverse Reactions Occurring in ≥ 1% of XIAFLEX-Treated Patients with Peyronie’s disease and at a Greater Incidence than Placebo After Up to Four Treatment Cycles in Studies 1 and 2 Combined
Adverse Reaction | XIAFLEX N=551 | Placebo N=281
All Adverse Reactions | 84.2% | 36.3%
Penile hematomaa | 65.5% | 19.2%
Penile swellingb | 55.0% | 3.2%
Penile painc | 45.4% | 9.3%
Penile ecchymosesd | 14.5% | 6.8%
Blood blister | 4.5% | 0
Penile blister | 3.3% | 0
Pruritus genital | 3.1% | 0
Painful erection | 2.9% | 0
Erectile dysfunction | 1.8% | 0.4%
Skin discoloration | 1.8% | 0
Procedural pain | 1.6% | 0.7%
Injection site vesicles | 1.3% | 0
Localized edema | 1.3% | 0
Dyspareunia | 1.1% | 0
Injection site pruritus | 1.1% | 0
Nodule | 1.1% | 0
Suprapubic pain | 1.1% | 0
a Includes: injection site hematoma and penile hematoma were reported with the verbatim term of penile bruising or injection site bruising in 87% of subjects.
b Includes: injection site swelling, penile edema, penile swelling, local swelling, scrotal swelling, and injection site edema.
c Includes: injection site pain, penile pain, and injection site discomfort.
d Includes: contusion, ecchymoses, penile hemorrhage, and injection site hemorrhage.

Severe penile hematoma or severe injection site hematoma were reported in 33/551 (6.0%) of XIAFLEX-treated patients and 0/281 (0%) of placebo-treated patients, in Studies 1 and 2 combined.

Reports of penile “popping” sounds or sensations
A popping noise or popping sensation in the penis, sometimes described as “snapping” or “cracking”, and sometimes accompanied by detumescence, hematoma and/or pain, were reported in 73/551 (13.2%) XIAFLEX-treated patients and 1/281 (0.3%) placebo-treated patients.

There were no clinically meaningful differences in the incidence of adverse events following treatment with XIAFLEX based on the severity of baseline erectile dysfunction or concomitant phosphodiesterase type 5 (PDE5) inhibitor use.

XIAFLEX was not associated with shortening of penile length in clinical trials in the treatment of Peyronie’s disease.

6.3 Immunogenicity

During clinical studies in Dupuytren’s contracture and Peyronie’s disease, patients were tested at multiple time points for antibodies to the protein components of XIAFLEX (AUX-I and AUX-II).

In the Dupuytren’s contracture clinical studies (Studies 1 and 2), at 30 days post the first injection of XIAFLEX 0.58 mg, 92% of patients had antibodies against AUX-I detected and 86% of patients had antibodies against AUX-II detected. After the fourth injection of XIAFLEX, every XIAFLEX-treated patient developed high titers of antibodies to both AUX-I and AUX-II. After 5 years more than 90% of patients remained seropositive for anti-AUX-I and anti-AUX-II antibody (Study 4). Neutralizing antibodies were assayed for all patients (204) in Study 1. Neutralizing antibodies to AUX-I or AUX-II, were detected in 10% and 21%, respectively, of patients treated with XIAFLEX. Among patients in Study 3 who reported no prior exposure to XIAFLEX, 97% of patients had antibodies against AUX-I and AUX-II after two concurrent doses of XIAFLEX 0.58 mg (total dose of 1.16 mg) in the same hand. In Study 5, treatment of recurrent contractures with XIAFLEX resulted in similar immunogenicity results as seen in Studies 1 and 2.

In the Peyronie’s disease clinical studies, at 6 weeks after the first treatment cycle of XIAFLEX 0.58 mg, approximately 75% of patients had antibodies against AUX-I and approximately 55% of patients had antibodies against AUX-II. Six weeks after the eighth injection (fourth treatment cycle) of XIAFLEX, >99% of XIAFLEX-treated patients developed high titers of antibodies to both AUX-I and AUX-II. Neutralizing antibodies were assayed for a subset of 70 samples selected to be representative of high and low titer binding antibody responses at Week 12 of treatment. For each subject in whom a Week 12 sample was selected, the corresponding Week 6, 18, 24, and 52 samples were assayed if they were also binding antibody positive. Neutralizing antibodies to AUX-I or AUX-II, were detected in 60% and 51.8%, respectively, of patients tested.

In patients treated for these two indications, there was no apparent correlation of antibody frequency, antibody titers, or neutralizing status to clinical response or adverse reactions.

Since the protein components in XIAFLEX (AUX-I and AUX-II) have some sequence homology with human matrix metalloproteinases (MMPs), anti-product antibodies could theoretically interfere with human MMPs. In vitro studies showed no evidence of cross-reactivity between anti-drug-antibody positive patient sera and a series of relevant MMPs. In addition, no clinical safety concerns related to the inhibition of endogenous MMPs have been observed.

Immunogenicity assay results are highly dependent on the sensitivity and specificity of the assay used in detection and may be influenced by several factors, including sample handling, timing of sample collection, concomitant medications, and underlying disease. For these reasons, comparison of incidence of antibodies to collagenase clostridium histolyticum with the incidence of antibodies to other products may be misleading.

6.4 Postmarketing Experience

The following adverse reactions have been identified during post-approval use of XIAFLEX. Because these reactions are reported voluntarily from a population of uncertain size, it is not always possible to reliably estimate their frequency or establish a causal relationship to drug exposure.

Acute Lower Back Pain Reactions

Reports of acute lower back pain reactions, sometimes accompanied by radiation of pain to the lower extremities, chest and arms, muscle spasms, chest pain, paresthesias and dyspnea, have been received involving patients treated with XIAFLEX for Peyronie’s disease. Some patients have also experienced temporary gait instability and an inability to ambulate for brief periods of time post injection. These events have occurred in close temporal proximity to XIAFLEX treatments. During retreatment injections with XIAFLEX, cases of recurrent acute lower back pain reactions have been reported. These events can be mild to severe in intensity. The events typically resolved within 15 minutes, but some lasted up to 30 minutes, and one event lasted 1.5 hours. The events typically did not require intervention, but some required observation and treatment with analgesics. The events typically resolved without sequelae, but in one event, pain improved but did not resolve at the time of final report.

Skin and Soft Tissue Necrosis Events

Reports of localized skin and soft tissue necrosis, occurring as sequelae of penile hematoma, have been received in patients treated with XIAFLEX for Peyronie’s disease. Some of the cases required surgical intervention.

Syncope and Presyncope

Cases of syncope and presyncope have been reported in the postmarketing period in patients treated with XIAFLEX. Potential triggers for the syncopal events, including post-procedure pain, suggest a vasovagal mechanism. Most, but not all the cases, occurred in the immediate treatment period or within 1 to 2 days following injection. Bodily injuries, including concussion, head abrasion, and other accidental injuries, have been reported in association with the syncopal events.

7 DRUG INTERACTIONS

Anticoagulant drugs: XIAFLEX should be used with caution in patients receiving concomitant anticoagulants (except for low-dose aspirin) [see Warnings and Precautions (5.5)].

8 USE IN SPECIFIC POPULATIONS

8.1 Pregnancy

Pregnancy Category B
There are no adequate and well-controlled studies of XIAFLEX in pregnant women. Because animal reproduction studies are not always predictive of human response, XIAFLEX should be used during pregnancy only if clearly needed.

Risk Summary
Based on animal data, XIAFLEX is not predicted to increase the risk for major developmental abnormalities in humans.

Human Data
Human pharmacokinetic studies showed that XIAFLEX levels were not quantifiable in the systemic circulation following injection into a Dupuytren’s cord.

Low levels of XIAFLEX were quantifiable in the plasma of evaluable male subjects for up to 30 minutes following administration of XIAFLEX into the penile plaque of subjects with Peyronie’s disease [see Clinical Pharmacology (12.3)].

Almost all patients develop anti-product antibodies (anti-AUX-I and anti-AUX-II) after treatment with XIAFLEX, and the clinical significance of anti-product antibody formation on a developing fetus is not known [see Adverse Reactions (6)].

Animal Data
Reproduction studies have been performed in rats with intravenous exposures up to approximately 11 times the maximum recommended human dose (MRHD) of XIAFLEX on a mg/m^2 basis, and have revealed no evidence of impaired fertility or harm to the fetus due to collagenase clostridium histolyticum.

8.3 Nursing Mothers

It is not known whether collagenase clostridium histolyticum is excreted in human milk. Because many drugs are excreted in human milk, caution should be exercised when XIAFLEX is administered to a nursing woman.

8.4 Pediatric Use

The safety and effectiveness of XIAFLEX in pediatric patients less than 18 years old have not been established.

8.5 Geriatric Use

Of the 249 XIAFLEX-treated patients in the double-blind, placebo-controlled, clinical trials in Dupuytren’s contracture (Studies 1 and 2), 104 (42%) were 65 years of age or older and 9% were 75 years of age or older. Of the 551 XIAFLEX-treated patients in the double-blind, placebo-controlled, clinical trials in Peyronie’s disease (Studies 1 and 2), 100 (18%) were 65 years of age or older and 5 (0.9 %) were 75 years of age or older. No overall differences in safety or effectiveness of XIAFLEX were observed between these patients and younger patients.

10 OVERDOSAGE

The effects of overdose of XIAFLEX are unknown. It is possible that multiple simultaneous or excessive doses of XIAFLEX may cause more severe local effects than the recommended doses including serious adverse reactions in the injected area (e.g., tendon ruptures or corporal ruptures dependent on the injection site). Supportive care and symptomatic treatment are recommended in these circumstances.

11 DESCRIPTION

XIAFLEX contains purified collagenase clostridium histolyticum, consisting of two microbial collagenases in a defined mass ratio, Collagenase AUX-I and Collagenase AUX-II, which are isolated and purified from the fermentation of Clostridium histolyticum bacteria.

Collagenase AUX-I is a single polypeptide chain consisting of approximately 1000 amino acids of known sequence. It has an observed molecular weight of 114 kiloDaltons (kDa). It belongs to the class I Clostridium histolyticum collagenases.

Collagenase AUX-II is a single polypeptide chain consisting of approximately 1000 amino acids of deduced sequence. It has an observed molecular weight of 113 kDa. It belongs to the class II Clostridium histolyticum collagenases.

XIAFLEX is supplied as a sterile lyophilized powder (white cake) intended for reconstitution with the supplied sterile diluent (0.3 mg/mL calcium chloride dihydrate in 0.9% sodium chloride) prior to intralesional injection into a Dupuytren’s cord or a Peyronie’s plaque.

XIAFLEX is available in single-use, glass vials containing 0.9 mg of collagenase clostridium histolyticum. Each vial also contains 0.5 mg of hydrochloric acid, 18.5 mg of sucrose, and 1.1 mg of tromethamine.

12 CLINICAL PHARMACOLOGY

12.1 Mechanism of Action

Collagenases are proteinases that hydrolyze collagen in its native triple helical conformation under physiological conditions, resulting in lysis of collagen deposits.

Injection of XIAFLEX into a Dupuytren’s cord, which is comprised mostly of collagen, may result in enzymatic disruption of the cord.

The signs and symptoms of Peyronie’s disease are caused by a collagen plaque. Injection of XIAFLEX into a Peyronie’s plaque, which is comprised mostly of collagen, may result in enzymatic disruption of the plaque. Following this disruption of the plaque, penile curvature deformity and patient bother caused by Peyronie’s disease are reduced [see Clinical Studies (14.2)].

Results of in vitro studies, including those of explant tissues containing Peyronie’s plaques, suggest that XIAFLEX disrupts the predominant collagen found in plaques (Types I and III). At higher doses and longer incubation times, non-fibrillar Type IV collagen was affected causing collagen lysis in small veins, but did not cause structural damage to arteries, nerves or large veins which contain Type IV collagen in in vitro or in vivo studies.

Results of in vitro studies suggest that the collagenases (AUX-I and AUX-II) worked synergistically to provide hydrolyzing activity towards collagen. However, there are no clinical data regarding the relative contributions of the individual collagenases (AUX-I or AUX-II) to the efficacy of XIAFLEX in the treatment of Dupuytren’s contracture or Peyronie’s disease.

Collagen fragments generated from clostridial collagenase have been shown to generate increased vascular permeability, inflammatory responses, and regenerative changes. However, the effects of the formation of the collagen fragments derived from the collagen plaque are unknown.

12.3 Pharmacokinetics

Following administration of either a single injection of XIAFLEX 0.58 mg into a Dupuytren’s cord in 20 patients or two concurrent injections of XIAFLEX 0.58 mg into Dupuytren’s cords of 12 patients, no quantifiable levels of XIAFLEX (AUX-I or AUX-II) were detected in plasma up to 30 days post injection.

Following each of two intralesional administrations, separated by 24 hours, of XIAFLEX 0.58 mg into the penile plaque of 19 subjects with Peyronie’s disease, plasma levels of AUX-I and AUX-II in subjects with quantifiable levels (79% and 40% for AUX-I and AUX-II, respectively) were minimal and short-lived. The maximal plasma concentrations of AUX-I and AUX-II were <29 ng/mL and <71 ng/mL, respectively, and were observed approximately within 10 minutes after injection. All plasma levels were below the limits of quantification within 30 minutes following dosing. There was no evidence of accumulation following two sequential injections of XIAFLEX administered 24 hours apart. No subject had quantifiable plasma levels 15 minutes after modeling of plaque on Day 3 (i.e., 24 hours after Injection 2 on Day 2).

13 NONCLINICAL TOXICOLOGY

13.1 Carcinogenesis, Mutagenesis, Impairment of Fertility

Carcinogenesis
Long-term animal studies to evaluate the carcinogenic potential of collagenase clostridium histolyticum have not been conducted.

Mutagenesis
Purified collagenase clostridium histolyticum was not mutagenic in Salmonella typhimurium (AMES test) and was not clastogenic in both an in vivo mouse micronucleus assay and an in vitro chromosomal aberration assay in human lymphocytes.

Impairment of Fertility
Collagenase clostridium histolyticum did not impair fertility and early embryonic development when administered intravenously in rats at exposures up to approximately 11 times the MRHD on a mg/m^2 basis.

13.2 Animal Toxicology and/or Pharmacology

Single or repeat-dose intravenous studies of collagenase clostridium histolyticum in rats were conducted to evaluate the toxicological impact of injection of collagenase clostridium histolyticum directly into the systemic circulation. Dose-dependent liver toxicity was noted at exposures greater than or equal to approximately 11 times the MRHD on a mg/m^2 basis as characterized by elevated aspartate aminotransferase (AST) and alanine aminotransferase (ALT) levels, increased liver weights, mild regenerative anemia with secondary changes in the spleen and histologic findings of chronic active inflammation, hemorrhage/hematoma, fibrosis, bile duct hyperplasia and/or hepatocellular necrosis. The histologic findings remained unresolved following a 2-week recovery period, while the other findings resolved completely. Animals that were found dead or prematurely euthanized had histopathological findings of hemorrhage and necrosis in the liver and extramedullary hematopoiesis in the liver and/or spleen. Death occurred at approximately 25 times the MRHD on a mg/m^2 basis between study days 7 and 15 following 8 repeat intravenous administrations of collagenase clostridium histolyticum over 16 days or after single intravenous doses at approximately 40 times the MRHD on a mg/m^2 basis.

In intermittent 13-week subcutaneous repeat-dose studies in rats or dogs administered doses up to approximately 3 times the MRHD on a mg/m^2 basis, respectively, there was no evidence of systemic toxicity. In a single-dose phase or 61-day repeat-dose phase (3 times a week every 3 weeks for 3 cycles) study of intrapenile administration of collagenase clostridium histolyticum in dogs at exposures lower than or equal to the MRHD on a mg/m^2 basis, there was no evidence of systemic toxicity.

14 CLINICAL STUDIES

14.1 Dupuytren’s Contracture

The efficacy of 0.58 mg of XIAFLEX was evaluated in two randomized, double-blind, placebo-controlled, multicenter trials in 374 adult patients with Dupuytren’s contracture (Studies 1 and 2). At study entry, patients must have had: (1) a finger flexion contracture with a palpable cord of at least one finger (other than the thumb) of 20 to 100 degrees in a metacarpophalangeal (MP) joint or 20 to 80 degrees in a proximal interphalangeal (PIP) joint and (2) a positive “table top test” defined as the inability to simultaneously place the affected finger(s) and palm flat against a table top. Patients could not have received a surgical treatment (e.g., fasciectomy, fasciotomy) on the selected primary joint within 90 days before the first injection of study medication and patients could not have received anticoagulation medication (except for up to 150 mg of aspirin per day) within 7 days before the first injection of study medication.

The cord affecting the selected primary joint received up to 3 injections of 0.58 mg of XIAFLEX or placebo on Days 0, 30, and 60. About 24 hours after each injection of study medication, if needed, the investigator manipulated (extended) the treated finger in an attempt to facilitate rupture of the cord (finger extension procedure). Following manipulation, patients were fitted with a splint, instructed to wear the splint at bedtime for up to 4 months, and instructed to perform a series of finger flexion and extension exercises each day.

Table 6 shows the baseline disease characteristics of patients with Dupuytren’s contracture in Studies 1 and 2.

Table 6. Baseline Disease Characteristics of Patients with Dupuytren’s Contracture
 | Study 1 | Study 2
Proportion of patients with prior surgery for Dupuytren’s contracture^1 | 38% | 53%
Proportion of patients with prior surgery for Dupuytren’s contracture on the same finger as the primary joint^1 | 8% | 18%
Mean number of affected joints | 3.0 | 3.3
^1 Prior surgery for Dupuytren’s contracture included fasciotomy and fasciectomy.

In Studies 1 and 2, the primary endpoint was to evaluate the proportion of patients who achieved a reduction in contracture of the selected primary joint (MP or PIP) to within 0 to 5 degrees of normal, 30 days after the last injection of that joint on Days 30, 60, or 90 (after up to 3 injections). As shown in Table 7, a greater proportion of XIAFLEX-treated patients compared to placebo-treated patients achieved the primary endpoint.

Table 7. Percentage of Patients Who Achieved Reduction in Contracture of the Primary Joint to 0° to 5° After Up to 3 Injections in Studies 1 and 2a
Treated Joint | Study 1 |  | Study 2
Treated Joint | XIAFLEXb | Placebo | XIAFLEXb | Placebo
All Joints (MP and PIP)c,d Difference (CIe) | N=203 | N=103 | N=45 | N=21
All Joints (MP and PIP)c,d Difference (CIe) | 64% 57% (47%, 67%) | 7% - | 44% 40% (14%, 62%) | 5% -
MP Jointsc Difference (CIe) | N=133 | N=69 | N=20 | N=11
MP Jointsc Difference (CIe) | 77% 69% (57%, 79%) | 7% - | 65% 56% (19%, 83%) | 9% -
PIP Jointsd Difference (CIe) | N=70 | N=34 | N=25 | N=10
PIP Jointsd Difference (CIe) | 40% 34% (14%, 52%) | 6% - | 28% 28% (-10%, 61%) | 0% -
a Patients may have received up to 3 injections of study medication into the cords associated with contracture of the primary joints on Days 0, 30, and 60. Assessments were made 30 days after the last injection (on Days 30, 60, or 90).
b For XIAFLEX-treated patients, the mean (±SD) number of injections given to the cord associated with the contracture was 1.7 (±0.8) in the 90-day controlled period in each trial.
c MP joints are metacarpophalangeal joints.
d PIP joints are proximal interphalangeal joints.
e 95% confidence interval.

The proportion of patients who achieved a contracture reduction of the primary joint to 0 to 5 degrees after the first injection was 39% and 1% in Study 1 and 27% and 5% in Study 2 in the XIAFLEX and placebo groups respectively.

XIAFLEX-treated patients, compared to placebo-treated patients, showed a greater increase from baseline in the range of motion of MP and PIP joints (see Table 8).

Table 8. Mean Increase in Range of Motion from Baseline in Degrees After Up to 3 Injections in Studies 1 and 2a
Treated Joint | Study 1 |  | Study 2
Treated Joint | XIAFLEX | Placebo | XIAFLEX | Placebo
All Joints b,c | N=196 | N=102 | N=45 | N=21
Baseline | 44 (20) | 45 (19) | 40 (15) | 44 (16)
Final | 80 (20) | 50 (22) | 76 (18) | 52 (20)
Increase | 36 (21) | 4 (15) | 35 (18) | 8 (15)
MP Joints b | N=129 | N=68 | N=20 | N=11
Baseline | 43 (20) | 46 (19) | 40 (12) | 41 (21)
Final | 83 (16) | 50 (21) | 80 (11) | 50 (22)
Increase | 41 (20) | 4 (13) | 40 (13) | 9 (15)
PIP Joints c | N=67 | N=34 | N=25 | N=10
Baseline | 46 (20) | 44 (18) | 41 (18) | 47 (10)
Final | 75 (24) | 49 (24) | 73 (21) | 54 (18)
Increase | 28 (22) | 5 (19) | 32 (20) | 7 (16)
aPatients may have received up to 3 injections of study medication into the cords associated with contracture of the primary joints on Days 0, 30, and 60. Assessments were made 30 days after the last injection (on Days 30, 60, or 90). Baseline and final range of motion degree values are expressed in mean (SD).
bMP = Metacarpophalangeal joint
cPIP = Proximal interphalangeal joint
Range of Motion = Degrees of Full Flexion minus Degrees of Fixed Extension
Not all patients had range of motion values at both time points.

Recurrence

A long-term, observational, Year 2 to Year 5, follow-up study (Study 4) was undertaken to evaluate recurrence of contracture and long-term safety in subjects who received up to 8 single injections of XIAFLEX 0.58 mg in a previous Phase 3 open-label or double-blind with open-label extension study. Of the 950 patients eligible for Study 4, only 645 patients enrolled. Of the 645 patients enrolled, 30% discontinued the study. Recurrence was assessed in successfully treated joints (i.e., subjects had a reduction in contracture to 5 degrees or less at the Day 30 evaluation after the last injection of XIAFLEX in a previous study) and was defined as an increase in joint contracture by at least 20 degrees in the presence of a palpable cord, or the joint underwent medical or surgical intervention primarily to correct a new or worsening Dupuytren’s contracture in that joint. Data on remaining recurrence free following successful treatment with XIAFLEX are provided in Figure 1.

Figure 1. Kaplan-Meier Plot Displaying Estimated Probability of Remaining Recurrence-Free over Time in the Observational Study 4 Among Joints That Were Successfully Treated in a Previous Study

Retreatment of Recurrent Contractures

Study 5 retreated a subset of patients from Study 4 for a joint that was previously successfully treated but had recurrence. Patients in Study 5 received up to 3 injections of XIAFLEX (0.58 mg). Of the 91patients eligible for Study 5, 52 patients enrolled. In Study 5, 65% of recurrent MP joints and 45% of recurrent PIP joints achieved clinical success after retreatment with up to three injections of XIAFLEX. There was no control group for comparison in Study 5.

14.2 Peyronie’s Disease

The efficacy of XIAFLEX was evaluated in two randomized, double-blind, placebo-controlled, multi-centered trials in 832 adult males with Peyronie’s disease (Studies 1 and 2). At study entry, patients must have had penile curvature deformity of at least 30 degrees in the stable phase of Peyronie’s disease. Patients were excluded if they had a ventral curvature deformity, an isolated hourglass deformity or a calcified plaque that could have interfered with the injection technique. At baseline, penile pain was either not present or was mild in most (98%) patients.

In these trials, patients were given up to 4 treatment cycles of XIAFLEX or placebo (weeks 0, 6, 12, 18), and were followed in a non-treatment follow-up period (weeks 24 - 52). In each treatment cycle, two injections of XIAFLEX or two injections of placebo were administered 1 to 3 days apart. A penile modeling procedure was performed on patients at the study site 1 to 3 days after the second injection of the cycle. The treatment cycle was repeated at approximately 6-week intervals for up to 3 additional times, for a maximum of 8 total injection procedures and 4 total modeling procedures. In addition, patients were instructed to perform penile modeling at home for 6 weeks after each treatment cycle [see Medication Guide].

Table 9 shows the baseline disease characteristics of patients with Peyronie’s disease in Studies 1 and 2.

Table 9. Baseline Disease Characteristics of Patientsa with Peyronie’s Disease (PD)
 | Study 1 |  | Study 2
 | XIAFLEX N=277 | Placebo N=140 | XIAFLEX N=274 | Placebo N=141
Mean age (years) (Min-Max) | 57.9 (28 - 79) | 58.2 (30 - 81) | 57.3 (23 - 84) | 57.6 (33 - 78)
Mean duration of PD (years) (Min-Max) | 3.9 (1.0 - 35.9) | 4.8 (1.0 - 50.8) | 4.2 (1.1 - 30.9) | 3.4 (1.1 - 47.1)
Mean Penile Curvature Deformity (degrees) (Min-Max) | 48.8 (30-90) | 49.0 (30-89) | 51.3 (30-90) | 49.6 (30-85)
Peyronie’s Disease Questionnaire (PDQ) b, – Mean Patient-Reported PD Bother Domain Score (range: 0-16) c | 7.5 | 7.4 | 7.4 | 8.4
History of Erectile Dysfunction N (%) | 128 (46.2) | 75 (53.6) | 134 (48.9) | 76 (53.9)
a Subjects were from intent-to-treat (ITT) population and received at least one dose of study drug in Study 1 or 2.
b Each PDQ assessment required subjects to have had vaginal intercourse in the 3 months prior to completion.
c Higher scores represent worse symptoms.

Before the first dose of study drug was administered, eligible subjects were stratified by the degree of curvature deformity (30 to 60 degrees, and 61 to 90 degrees) and then randomized into two treatment groups to receive either XIAFLEX or placebo in a 2:1 ratio. The efficacy population (modified intent-to-treat [mITT] population) comprised a total of 612 intent-to-treat subjects (ITT) who had both a curvature deformity measurement and a Peyronie's disease questionnaire (PDQ) assessment at baseline, and at one or more subsequent time points in Studies 1 and 2, and had engaged in vaginal intercourse within 3 months prior to each PDQ assessment.

In Studies 1 and 2, the co-primary endpoints were:

- the percent change from baseline to Week 52 in penile curvature deformity and;
- the change from baseline to Week 52 in the Bother domain score of the PDQ

The Bother domain score is a composite of the following patient-reported items: concern about erection pain, erection appearance, and the impact of Peyronie’s disease on intercourse and on frequency of intercourse.

Penile Curvature Deformity (Co-primary Endpoint)
XIAFLEX treatment significantly improved penile curvature deformity in patients with Peyronie’s disease compared with placebo (see Table 10). The improvement in curvature deformity was numerically similar among subjects with baseline curvature deformity from 30 to 60 degrees and those with curvature deformity from 61 to 90 degrees.

Table 10. Mean Percent Change in Penile Curvature Deformity from Baseline to Week 52 - Studies 1 and 2
 | Study 1 |  | Study 2
 | XIAFLEX N=199 | Placebo N=104 | XIAFLEX N=202 | Placebo N=107
Baseline Mean (degrees) | 48.8° | 49.0° | 51.3° | 49.6°
Mean Percent Change a | -35.0% | -17.8% | -33.2% | -21.8%
Treatment Difference (95% CI) | -17.2%b (-26.7%, -7.6%) |  | -11.4% b (-19.5%, -3.3%)
a Mean percent change, treatment difference, 95% CI, and p value were based on an analysis of variance (ANOVA) model with factors for treatment, stratum of baseline penile curvature, and their interaction and using last observation carried forward (LOCF) in the modified intent-to-treat (mITT) population. The mITT population was defined as all randomized subjects who had both a penile curvature deformity measurement and a Peyronie's disease questionnaire (PDQ) assessment at baseline and at one or more subsequent time points.
b p value < 0.01

Figure 2. Mean Percent Change in Penile Curvature Deformity –Study 1

Analysis of variance (ANOVA) model - adjusted values with factors for treatment, stratum of baseline penile curvature, and their interaction and using last observation carried forward (LOCF) in the modified intent-to-treat (mITT) population.

Figure 3. Mean Percent Change in Penile Curvature Deformity – Study 2

Analysis of variance (ANOVA) model - adjusted values with factors for treatment, stratum of baseline penile curvature, and their interaction and using last observation carried forward (LOCF) in the modified intent-to-treat (mITT) population.

Peyronie’s Disease Questionnaire Bother Domain Score (Co-primary Endpoint)
XIAFLEX significantly reduced patient-reported bother associated with Peyronie’s disease compared with placebo (see Table 11). The reduction in the bother domain score was numerically similar between patient groups stratified by degree of baseline curvature deformity (30 to 60 degrees, and 61 to 90 degrees).

Table 11. Mean Change in Peyronie’s Disease Bother Domain Score from Baseline to Week 52 – Studies 1 and 2
 | Study 1 |  | Study 2
 | XIAFLEX N=199 | Placebo N=104 | XIAFLEX N=202 | Placebo N=107
Baseline Mean | 7.5 | 7.4 | 7.4 | 8.2
Mean Change a | -2.8 | -1.6 | -2.6 | -1.5
Treatment Difference (95% CI) | -1.2b (-2.4, -0.03) |  | -1.1b (-2.1, -0.002)
a Mean change, treatment difference, 95% CI, and p value all based on an analysis of variance (ANOVA) model with factors for treatment, stratum of baseline penile curvature, and their interaction and using last observation carried forward (LOCF) in the modified intent-to-treat (mITT) population. The mITT population was defined as all randomized subjects who had both a penile curvature deformity measurement and a Peyronie's disease questionnaire (PDQ) assessment at baseline and at one or more subsequent time points.
b p value < 0.05.

Figure 4. Mean Change in Patient-Reported Peyronie’s Disease Bother Domain Score – Study 1

Analysis of variance (ANOVA) model - adjusted values with factors for treatment, stratum of baseline penile curvature, and their interaction and using last observation carried forward (LOCF) in the modified intent-to-treat (mITT) population.

Figure 5. Mean Change in Patient-Reported Peyronie’s Disease Bother Domain Score – Study 2

Analysis of variance (ANOVA) model - adjusted values with factors for treatment, stratum of baseline penile curvature, and their interaction and using last observation carried forward (LOCF) in the modified intent-to-treat (mITT) population.

There were no clinically meaningful differences in the mean percent improvement in curvature deformity or mean reduction in the bother domain score following treatment with XIAFLEX based on the severity of baseline erectile dysfunction or concomitant phosphodiesterase type 5 (PDE5) inhibitor use.

16 HOW SUPPLIED/STORAGE AND HANDLING

XIAFLEX is available in single-use, glass vials containing 0.9 mg of collagenase clostridium histolyticum as a sterile, lyophilized powder.

Sterile diluent for reconstitution is available in single-use, glass vials containing 3 mL of 0.3 mg/mL calcium chloride dihydrate in 0.9% sodium chloride.

NDC Number | Package Size
66887-003-01 | Single-use package: 1 carton containing a single-use vial of XIAFLEX and a single-use vial of sterile diluent
66887-003-02 | Dual-Pack (2 single-use packages): 1 box containing 2 cartons, each containing a single-use vial of XIAFLEX and a single-use vial of sterile diluent

Storage and Stability
Prior to reconstitution, the vials of XIAFLEX and diluent should be stored in a refrigerator at 2°C to 8°C (36°F to 46°F). [see Dosage and Administration (2.1, 2.2)]. Do not freeze.

The reconstituted XIAFLEX solution can be kept at room temperature (20°C to 25°C/68°F to 77°F) for up to 1 hour or refrigerated at 2°C to 8°C (36°F to 46°F) for up to 4 hours prior to administration [see Dosage and Administration (2.1, 2.2)].

17 PATIENT COUNSELING INFORMATION

See FDA-approved patient labeling (Medication Guide).

17.1 Patient Counseling for Dupuytren’s Contracture

Advise patients of the following:

- Serious complications of XIAFLEX injection include tendon rupture, serious ligament damage, or skin laceration that may result in the inability to fully bend the finger and may require surgery to correct the complication.
- XIAFLEX injection is likely to result in swelling, bruising, bleeding, and/or pain of the injected site and surrounding tissue.

After the XIAFLEX injections, instruct patients:

- Not to flex or extend the fingers of the injected hand to reduce extravasation of XIAFLEX out of the cord(s).
- Not to attempt to disrupt the injected cord(s) by self-manipulation.
- To elevate the injected hand until bedtime.
- To promptly contact their physician if there is evidence of infection (e.g., fever, chills, increasing redness or edema), sensory changes in the treated finger(s), trouble bending the finger(s) after the swelling goes down (symptoms of tendon rupture), or skin laceration.
- To return to their healthcare provider’s office 1 to 3 days after the injection visit for an examination of the injected hand and for possible finger extension procedure(s) to disrupt the cord.

Following the finger extension procedure(s) and fitting patient with a splint, instruct patients:

- Not to perform strenuous activity with the injected hand until advised to do so.
- To wear the splint at bedtime for up to 4 months.
- To perform a series of finger flexion and extension exercises each day.

17.2 Patient Counseling for Peyronie’s Disease

Advise patients of the following:

- Serious complications of XIAFLEX injection include corporal rupture, penile hematoma and skin and soft tissue necrosis related to penile hematoma, and these events may require surgery to correct the complication.
- Acute post-injection back pain reactions have been reported in patients treated with XIAFLEX. Back pain may be mild to severe and may radiate to the legs, chest and arms, may include spasms, and may make walking difficult. Events typically resolve within 15 minutes but may last longer. Patients should report post-injection back pain reactions to their healthcare provider.

After the XIAFLEX injections, instruct the patient:

- That their penis may appear bruised and/or swollen
- That they may have mild-to-moderate penile pain that can be relieved by taking over-the-counter pain medications
- To promptly contact their physician if, at any time, they have severe pain or severe swelling of the penis, severe purple bruising and swelling of the penis, difficulty urinating or blood in the urine, or sudden loss of the ability to maintain an erection. These symptoms may be accompanied by a popping or cracking sound from the penis
- To return to their healthcare provider’s office when directed for further injection(s) and/or penile modeling procedure(s)
- To not have sex between the first and second injections of a treatment cycle
- To wait 4 weeks after the second injection of a treatment cycle before resuming sexual activity, provided pain and swelling have subsided
- To perform gentle, at home modeling activities, as recommended by their physician
- To refrain from using a vacuum erection device during treatment with XIAFLEX
- To avoid abdominal straining associated with situations, such as straining during bowel movements

Provide the patient instructions on the appropriate technique to perform penile modeling activities at home, as described in “What You Need to Know About XIAFLEX Treatment for Peyronie's Disease: A Patient Guide”, and give the patient a copy.

Manufactured by:
Endo USA
Rochester, MI 48307

US License No. 1816

US Patent Nos. 7,811,560; RE39,941; and 6,022,539

© 2024 Endo, Inc. or one of its affiliates.

Revised: 04/2024

Medication Guide
XIAFLEX® (Zī a flex)
(collagenase clostridium histolyticum)
For injection, for intralesional use

XIAFLEX is approved for two uses: Dupuytren's contracture and Peyronie's disease. Information is provided separately for each use. Use for treating Dupuytren's contracture is described first, followed by use for treating Peyronie's disease.

Read this Medication Guide before you receive XIAFLEX for the treatment of Dupuytren’s contracture and each time you get an injection. There may be new information. This Medication Guide does not take the place of talking with your healthcare provider about your medical condition or treatment.

What is the most important information I should know about XIAFLEX for the treatment of Dupuytren’s contracture?

XIAFLEX may cause serious side effects, including:

1. Tendon rupture or ligament damage. Receiving an injection of XIAFLEX may cause damage to a tendon or ligament in your hand and cause it to break or weaken. This could require surgery to fix the damaged tendon or ligament. Call your healthcare provider right away if you have trouble bending your injected finger (towards the wrist) after the swelling goes down or you have problems using your treated hand after your follow-up visit.
2. Nerve injury or other serious injury of the hand. After finger procedures, some people developed tears in the skin (lacerations), and local skin and soft-tissue necrosis (death of skin cells). Some lacerations and necrosis required skin grafting, or other surgery including amputation. Call your healthcare provider right away if you get numbness, tingling, increased pain, or tears in the skin (laceration) in your treated finger or hand after your injection or after your follow-up visit.
3. Hypersensitivity reactions, including anaphylaxis. Severe allergic reactions can happen in people who receive XIAFLEX, because it contains foreign proteins.

Call your healthcare provider right away if you have any of these symptoms of an allergic reaction after an injection of XIAFLEX:

- hives
- chest pain
- swollen face
- low blood pressure
- breathing trouble
- dizziness or fainting

4. Fainting: Fainting or near fainting can happen in people who receive XIAFLEX, especially following finger procedures.

If you have dizziness or feel faint after receiving XIAFLEX, lie down until the symptoms go away.

What is XIAFLEX?

XIAFLEX is a prescription medicine used to treat adults with Dupuytren’s contracture when a “cord” can be felt.
It is not known if XIAFLEX is safe and effective in children under the age of 18.

Who should not receive XIAFLEX?

Do not receive XIAFLEX if you:

- are allergic to collagenase clostridium histolyticum, or any of the ingredients in XIAFLEX, or to any other collagenase product. See the end of this Medication Guide for a complete list of ingredients in XIAFLEX.

Talk to your healthcare provider before receiving this medicine if you have any of these conditions.

What should I tell my healthcare provider before receiving XIAFLEX?

Before receiving XIAFLEX, tell your healthcare provider if you:

- have had an allergic reaction to a XIAFLEX injection in the past
- have a bleeding problem
- have received XIAFLEX to treat another condition
- have any other medical conditions
- are pregnant or plan to become pregnant. It is not known if XIAFLEX will harm your unborn baby.
- are breastfeeding or plan to breastfeed. It is not known if XIAFLEX passes into your breast milk. Talk to your healthcare provider about the best way to feed your baby if you receive XIAFLEX.

Tell your healthcare provider about all the medicines you take, including prescription and over-the-counter medicines, vitamins, and herbal supplements.

Using XIAFLEX with certain other medicines can cause serious side effects.

Especially tell your healthcare provider if you take:

- medicines to thin your blood (anticoagulants). If you are told to stop taking a blood thinner before your XIAFLEX injection, your healthcare provider should tell you when to restart the blood thinner.

Ask your healthcare provider or pharmacist for a list of these medicines, if you are not sure.

Know the medicines you take. Keep a list of them to show to your healthcare provider and pharmacist when you get a new medicine.

How will I receive XIAFLEX?

- XIAFLEX should be injected into a cord by a healthcare provider who is experienced in injection procedures of the hand and treating people with Dupuytren’s contracture. If you have more than 1 contracture, your healthcare provider may give you 2 injections in 1 of your hands during your visit.
- Your healthcare provider will inject XIAFLEX into the cord that is causing your finger to bend.
- After an injection of XIAFLEX, your affected hand will be wrapped with a bandage. You should limit moving and using the treated finger after the injection.
  - Do not bend or straighten the fingers of the injected hand until your healthcare provider says it is okay. This will help to keep the medicine from leaking out of the cord.
  - Do not try to straighten the treated finger yourself.
- Keep the injected hand elevated until bedtime.
- Call your healthcare provider right away if you have:
  - signs of infection after your injection, such as fever, chills, increased redness, or swelling
  - numbness or tingling in the treated finger
  - trouble bending the injected finger after the swelling goes down
- Return to your healthcare provider’s office as directed 1 to 3 days after your injection. During this first follow-up visit, if you still have the cord, your healthcare provider may try to extend the treated finger to “break” the cord and try to straighten your finger.
- Your healthcare provider will provide you with a splint to wear on the treated finger. Wear the splint as instructed by your healthcare provider at bedtime to keep your finger straight.
- Do finger exercises each day, as instructed by your healthcare provider.
- Follow your healthcare provider’s instructions about when you can start doing your normal activities with the injected hand.

What are the possible side effects of XIAFLEX?

XIAFLEX may cause serious side effects, including:

- See “What is the most important information I should know about XIAFLEX for the treatment of Dupuytren’s contracture?”
- increased chance of bleeding. Bleeding or bruising at the injection site can happen in people who receive XIAFLEX. Talk to your healthcare provider if you have a problem with your blood clotting. XIAFLEX may not be right for you.

The most common side effects with XIAFLEX for the treatment of Dupuytren’s contracture include:

- swelling of the injection site or the hand
- bruising or bleeding at the injection site
- pain or tenderness of the injection site or the hand
- swelling of the lymph nodes (glands) in the elbow or armpit (axilla)
- itching
- breaks in the skin
- redness or warmth of the skin
- pain in the armpit

Tell your healthcare provider if you have any side effect that bothers you or does not go away.

These are not all of the possible side effects with XIAFLEX. For more information, ask your healthcare provider or pharmacist.

Call your doctor for medical advice about side effects. You may report side effects to FDA at 1-800-FDA-1088.

General information about the safe and effective use of XIAFLEX.

Medicines are sometimes prescribed for purposes other than those listed in a Medication Guide.

This Medication Guide summarizes the most important information about XIAFLEX. If you would like more information, talk to your healthcare provider. You can ask your healthcare provider or pharmacist for information about XIAFLEX that is written for health professionals.

For more information, go to www.XIAFLEX.com or call 1-800-462-3636.

What are the ingredients in XIAFLEX?

Active ingredient: collagenase clostridium histolyticum

Inactive ingredients: hydrochloric acid, sucrose, and tromethamine. The diluent contains: calcium chloride dihydrate in 0.9% sodium chloride

This Medication Guide has been approved by the U.S. Food and Drug Administration.

Manufactured by:
Endo USA
Rochester, MI 48307

US License No. 1816

US Patent Nos. 7,811,560 and 6,022,539

© 2024 Endo, Inc. or one of its affiliates.

04/2024

Medication Guide
XIAFLEX® (Zī a flex)
(collagenase clostridium histolyticum)
For injection, for intralesional use

XIAFLEX is approved for two uses: Dupuytren's contracture and Peyronie's disease. Information is provided separately for each use. Use for treating Dupuytren's contracture is described on the previous pages, and use for treating Peyronie’s disease is described below.

Read this Medication Guide before you receive XIAFLEX for the treatment of Peyronie’s disease and each time you get an injection. There may be new information. This Medication Guide does not take the place of talking with your healthcare provider about your medical condition or treatment.

Your healthcare provider will also talk to you about receiving XIAFLEX for the treatment of Peyronie’s disease using the “What You Need to Know About XIAFLEX Treatment for Peyronie’s Disease: A Patient Guide”. You can ask your healthcare provider for a copy of the Patient Guide.

What is the most important information I should know about XIAFLEX for the treatment of Peyronie’s Disease?

XIAFLEX can cause serious side effects, including:

1. Penile fracture (corporal rupture) or other serious injury to the penis. Receiving an injection of XIAFLEX may cause damage to the tubes in your penis called the corpora. After treatment with XIAFLEX, one of these tubes may break during an erection. This is called a corporal rupture or penile fracture. This could require surgery to fix the damaged area. Damage to your penis might not get better after a corporal rupture.

- After treatment with XIAFLEX, blood vessels in your penis may also break, causing blood to collect under the skin (hematoma). This could require a procedure to drain the blood from under the skin. If a hematoma appears, you may also develop skin and soft tissue necrosis (death of skin cells) which could require surgery.
  Symptoms of corporal rupture or other serious injury to your penis may include:
  - a popping sound or sensation in an erect penis
  - sudden loss of the ability to maintain an erection
  - pain in your penis
  - purple bruising and swelling of your penis
  - difficulty urinating or blood in the urine

Call your healthcare provider right away if you have any of the symptoms of corporal rupture or serious injury to the penis listed above.

Do not have sex or any other sexual activity between the first and second injections of a treatment cycle.

Do not have sex or have any other sexual activity for at least 4 weeks after the second injection of a treatment cycle with XIAFLEX and after any pain and swelling has gone away.

XIAFLEX for the treatment of Peyronie’s disease is only available through a restricted program called the XIAFLEX Risk Evaluation and Mitigation Strategy (REMS) Program. For more information about the XIAFLEX REMS Program go to www.XIAFLEXREMS.com or call 1-877-313-1235.

2. Hypersensitivity reactions, including anaphylaxis. Severe allergic reactions can happen in people who receive XIAFLEX, because it contains foreign proteins.

Call your healthcare provider right away if you have any of these symptoms of an allergic reaction after an injection of XIAFLEX:

- hives
- chest pain
- swollen face
- low blood pressure
- breathing trouble
- dizziness or fainting

3. Back pain reactions. After receiving an injection of XIAFLEX for Peyronie’s disease, you may suddenly feel back pain, including severe lower back pain moving to your legs, feet, chest and arms. The back pain may also include spasms and make it hard to walk. These symptoms usually go away in 15 minutes or less but may last longer.

Tell your healthcare provider right away if you have sudden back pain, chest pain, or have a hard time walking after an injection.

4. Fainting: Fainting or near fainting can happen in people who receive XIAFLEX, especially if they have severe penile pain.

If you have dizziness or feel faint after receiving XIAFLEX, lie down until the symptoms go away.

What is XIAFLEX?

XIAFLEX is a prescription medicine used to treat adult men with Peyronie’s disease who have a “plaque” that can be felt and a curve in their penis greater than 30 degrees when treatment is started.

It is not known if XIAFLEX is safe and effective in children under the age of 18.

Who should not receive XIAFLEX?

Do not receive XIAFLEX if you:

- have been told by your healthcare provider that the Peyronie’s plaque to be treated involves the “tube” that your urine passes through (urethra).
- are allergic to collagenase clostridium histolyticum, or any of the ingredients in XIAFLEX, or to any other collagenase product. See the end of this Medication Guide for a complete list of ingredients in XIAFLEX.

Talk to your healthcare provider before receiving this medicine if you have any of these conditions.

What should I tell my healthcare provider before receiving XIAFLEX?

Before receiving XIAFLEX, tell your healthcare provider if you:

- have had an allergic reaction to a XIAFLEX injection in the past
- have a bleeding problem
- have received XIAFLEX to treat another condition
- have any other medical conditions

Tell your healthcare provider about all the medicines you take, including prescription and over-the-counter medicines, vitamins, and herbal supplements.

Using XIAFLEX with certain other medicines can cause serious side effects.

Especially tell your healthcare provider if you take:

- medicines to thin your blood (anticoagulants). If you are told to stop taking a blood thinner before your XIAFLEX injection, your healthcare provider should tell you when to start taking the blood thinner again.

Ask your healthcare provider or pharmacist for a list of these medicines, if you are not sure.

Know the medicines you take. Keep a list of them to show to your healthcare provider and pharmacist when you get a new medicine.

How will I receive XIAFLEX?

- XIAFLEX should be injected into the plaque by a healthcare provider who is trained and experienced in treating adult men with Peyronie’s disease.
- Your healthcare provider will inject XIAFLEX into the plaque that is causing your penis to curve.
- XIAFLEX is given as part of a treatment cycle. In each treatment cycle, you will receive an injection of XIAFLEX, followed by a second injection 1 to 3 days later.
- After each injection of XIAFLEX, your penis may be wrapped with a bandage. Your healthcare provider will tell you when to take the bandage off.
- 1 to 3 days after your second injection of XIAFLEX in a treatment cycle, you will need to return to your healthcare provider’s office for a manual procedure that will stretch and help straighten your penis. Your healthcare provider will tell you when to come back for this.
- Your healthcare provider will show you how to gently stretch your penis the right way. See “How to gently stretch your penis.”
- You should gently stretch your penis 3 times a day for 6 weeks after each treatment cycle. You should only gently stretch your penis when you do not have an erection.
- Your healthcare provider will show you how to gently straighten your penis the right way. See “How to gently straighten your penis.”
- You should gently straighten your penis 1 time a day for 6 weeks after each treatment cycle. You should only gently straighten your penis if you have an erection that happens without any sexual activity (spontaneous erection).
- Do not use a vacuum erection device during your treatment with XIAFLEX.
- Your healthcare provider will tell you when you can resume sexual activity after each treatment cycle.
- Your healthcare provider will also tell you when to come back if more treatment cycles are needed.

Tell your healthcare provider right away if you have trouble stretching or straightening your penis, or if you have pain or other concerns.

How to gently stretch your penis:

Gently stretch your penis 3 times a day. Only stretch your penis if your penis is not hard (erect).

- With 1 hand, hold the tip of your penis with your fingers. With your other hand, hold the base of your penis with your fingers (See Figure A).
- Gently pull your penis away from your body to its full length and hold the stretch for 30 seconds.
- Let go of the tip of your penis and let your penis return to its normal length.

(Figure A)

How to gently straighten your penis:

Gently straighten your penis 1 time a day. Only straighten your penis if you have an erection that happens without any sexual activity (spontaneous erection). Bending your penis should not cause any pain or discomfort.

- With 1 hand hold your penis. With your other hand, gently bend your penis in the opposite direction of the curve (See Figure B). Hold the penis in this more straightened position for 30 seconds, then let go.

(Figure B)

What should I avoid while receiving XIAFLEX?

Avoid situations that may cause you to strain your stomach (abdominal) muscles, such as straining during bowel movements.

What are the possible side effects of XIAFLEX?

XIAFLEX can cause serious side effects, including:

See “What is the most important information I should know about XIAFLEX for the treatment of Peyronie’s disease?”

- increased chance of bleeding. Bleeding or bruising at the injection site can happen in people who receive XIAFLEX. Talk to your healthcare provider if you have a problem with your blood clotting. XIAFLEX may not be right for you.

The most common side effects with XIAFLEX for the treatment of Peyronie’s disease include:

- a small collection of blood under the skin at the injection site (hematoma)
- swelling at the injection site or along your penis
- pain or tenderness at the injection site, along your penis and above your penis
- penis bruising
- itching of your penis or scrotum (genitals)
- painful erection
- erection problems (erectile dysfunction)
- changes in the color of the skin of your penis
- blisters at the injection site
- pain with sex
- a lump at the injection site (nodule)

Tell your healthcare provider if you have any side effect that bothers you or does not go away.

These are not all of the possible side effects with XIAFLEX. For more information, ask your healthcare provider or pharmacist.

Call your doctor for medical advice about side effects. You may report side effects to FDA at 1-800-FDA-1088.

General information about the safe and effective use of XIAFLEX.

Medicines are sometimes prescribed for purposes other than those listed in a Medication Guide.

This Medication Guide summarizes the most important information about XIAFLEX. If you would like more information, talk to your healthcare provider. You can ask your healthcare provider or pharmacist for information about XIAFLEX that is written for health professionals.

For more information, go to www.XIAFLEX.com or call 1-800-462-3636.

What are the ingredients in XIAFLEX?

Active ingredient: collagenase clostridium histolyticum

Inactive ingredients: hydrochloric acid, sucrose, and tromethamine. The diluent contains: calcium chloride dihydrate in 0.9% sodium chloride

Manufactured by:
Endo USA
Rochester, MI 48307

US License No. 1816

US Patent Nos. 7,811,560 and 6,022,539

© 2024 Endo, Inc. or one of its affiliates.

This Medication Guide has been approved by the U.S. Food and Drug Administration 04/2024

PACKAGE LABEL

Package Label - Principal Display Panel – 3 mL Vial, Sterile Diluent

PACKAGE LABEL

Package Label - Principal Display Panel – 0.9 mg Vial, XIAFLEX for Injection

Package Label - Principal Display Panel – Single-Pack Carton